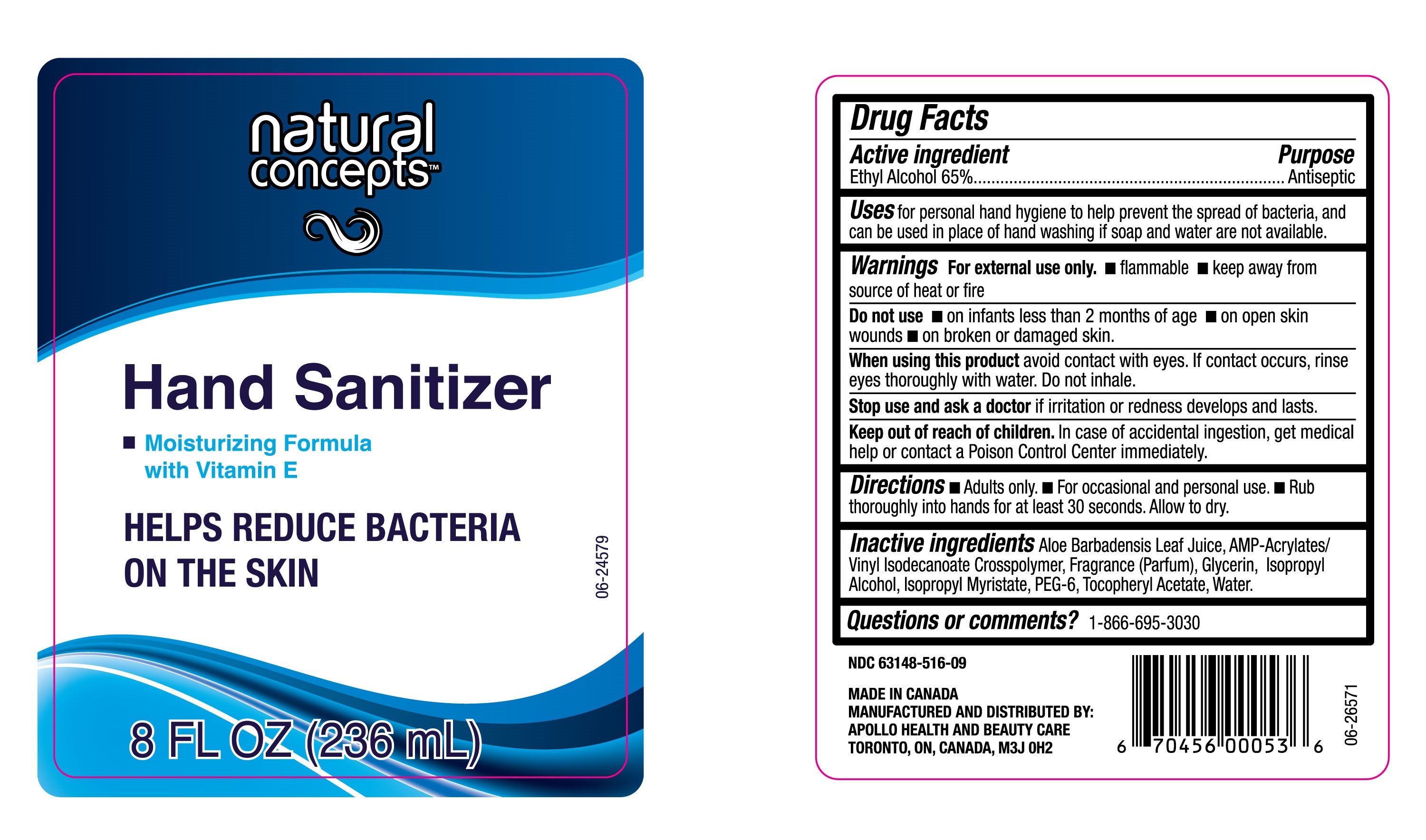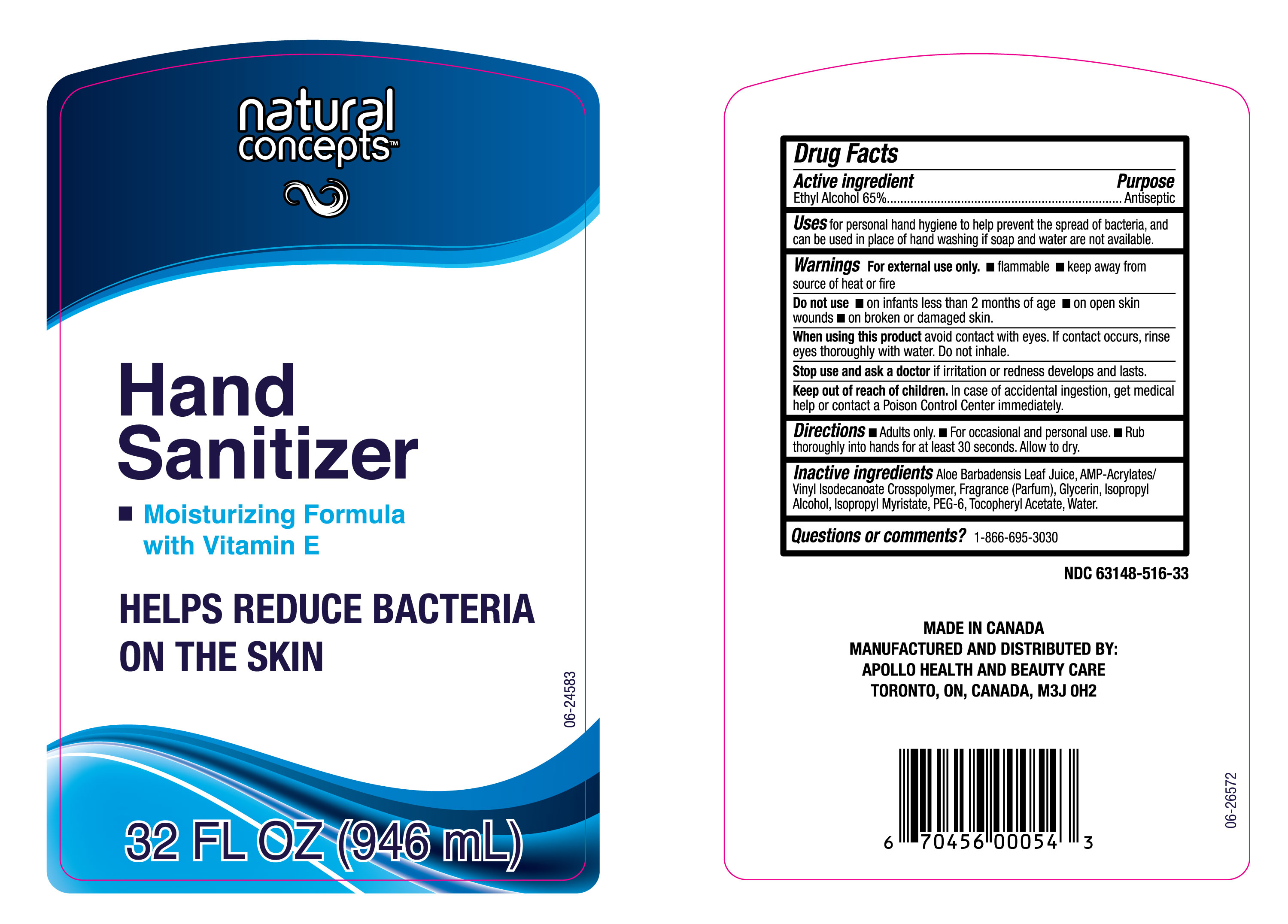 DRUG LABEL: Natural Concepts Hand Sanitizer
NDC: 63148-516 | Form: GEL
Manufacturer: Apollo Health and Beauty Care Inc.
Category: otc | Type: HUMAN OTC DRUG LABEL
Date: 20251117

ACTIVE INGREDIENTS: ALCOHOL 650 mg/1 mL
INACTIVE INGREDIENTS: FRAGRANCE CLEAN ORC0600327; ACRYLATES/VINYL ISODECANOATE CROSSPOLYMER (10000 MPA.S NEUTRALIZED AT 0.5%); WATER; PEG-6; ISOPROPYL ALCOHOL; GLYCERIN; ISOPROPYL MYRISTATE; ALOE VERA LEAF; .ALPHA.-TOCOPHEROL ACETATE, DL-

NDC-63148-516

Active Ingredient

Ethyl Alcohol (65%)

Purpose

Antiseptic

Uses

for personal hand hygiene to help prevent the spread of bacteria, and can be used in place of hand washing if soap and water are not available.

Warnings

For external use only.

- Flammable
- Keep away from source of heat or fire.

Do not use

- On infants less than 2 months of age
- On open skin wounds.
- On broken or damaged skin.

When using this Product

Avoid contact with eyes. If contact occurs, rinse eyes thoroughly with water. Do not inhale.

Stop use and ask a doctor

if irritation or redness develops and lasts.

Keep out of reach of children

In case of accidental ingestion, get medical help or contact a Poison Control Center immediately.

Directions

- Adults only
- For occasional and personal use
- Rub thoroughly into hands for at least 30 seconds. Allow to dry.

Inactive ingredients

Aloe Barbadensis Leaf Juice,,AMP-Acrylates/Vinyl Isodecanoate Crosspolymer, Fragrance (Parfum), Glycerin, Isopropyl Alcohol, Isopropyl Myristate, PEG-6, Tocopheryl Acetate, Water.

Questions or comments?

1-866-695-3030